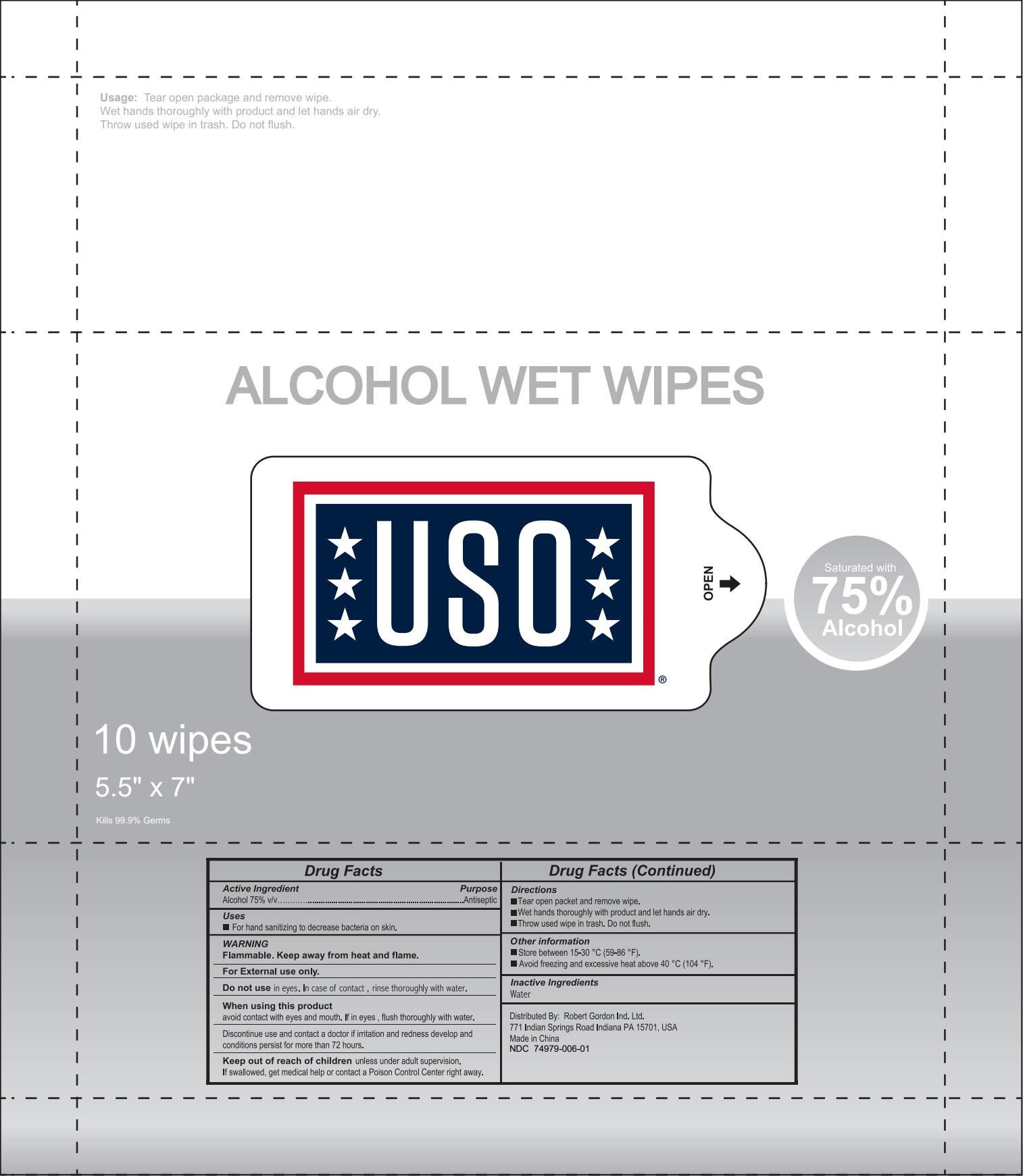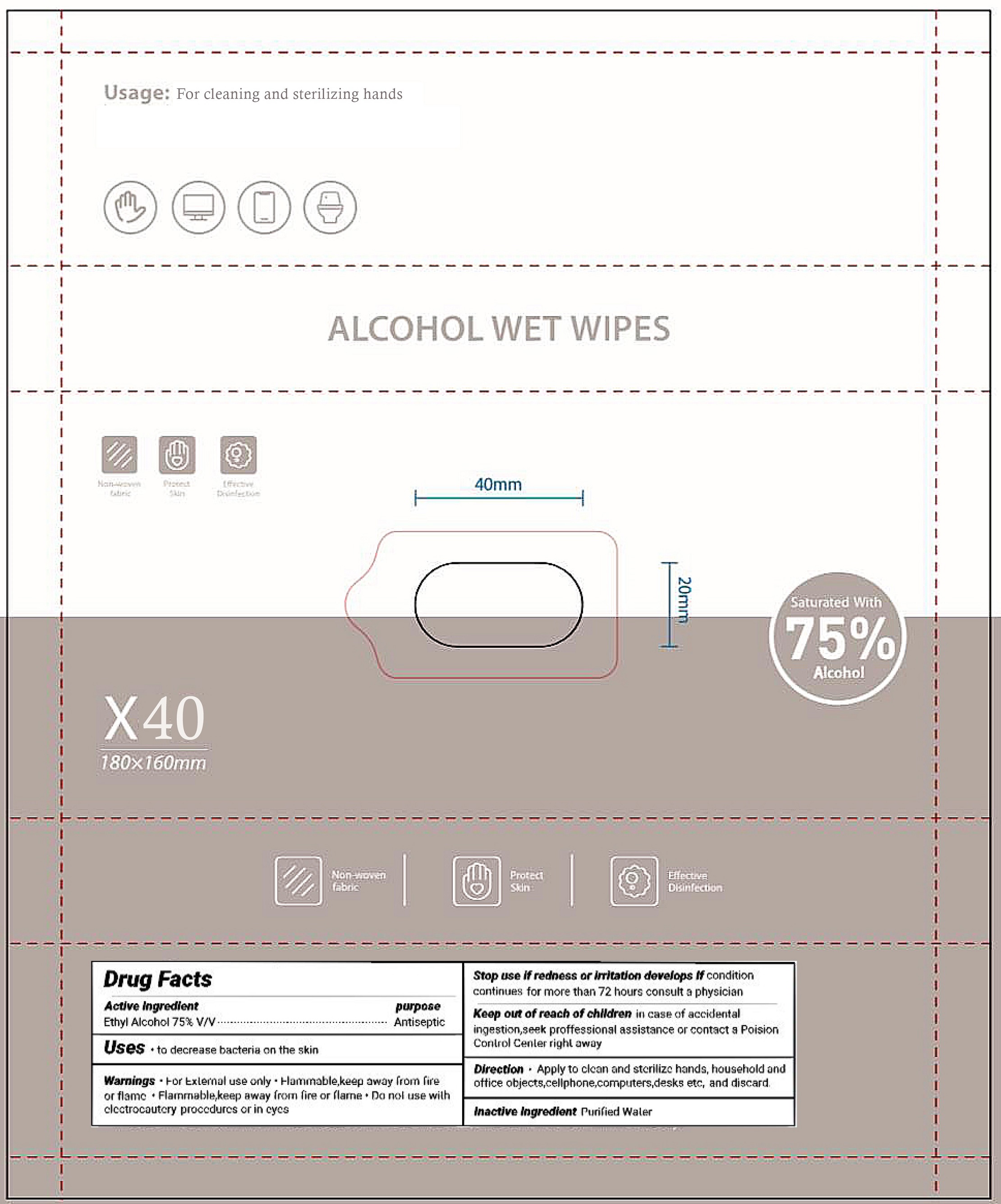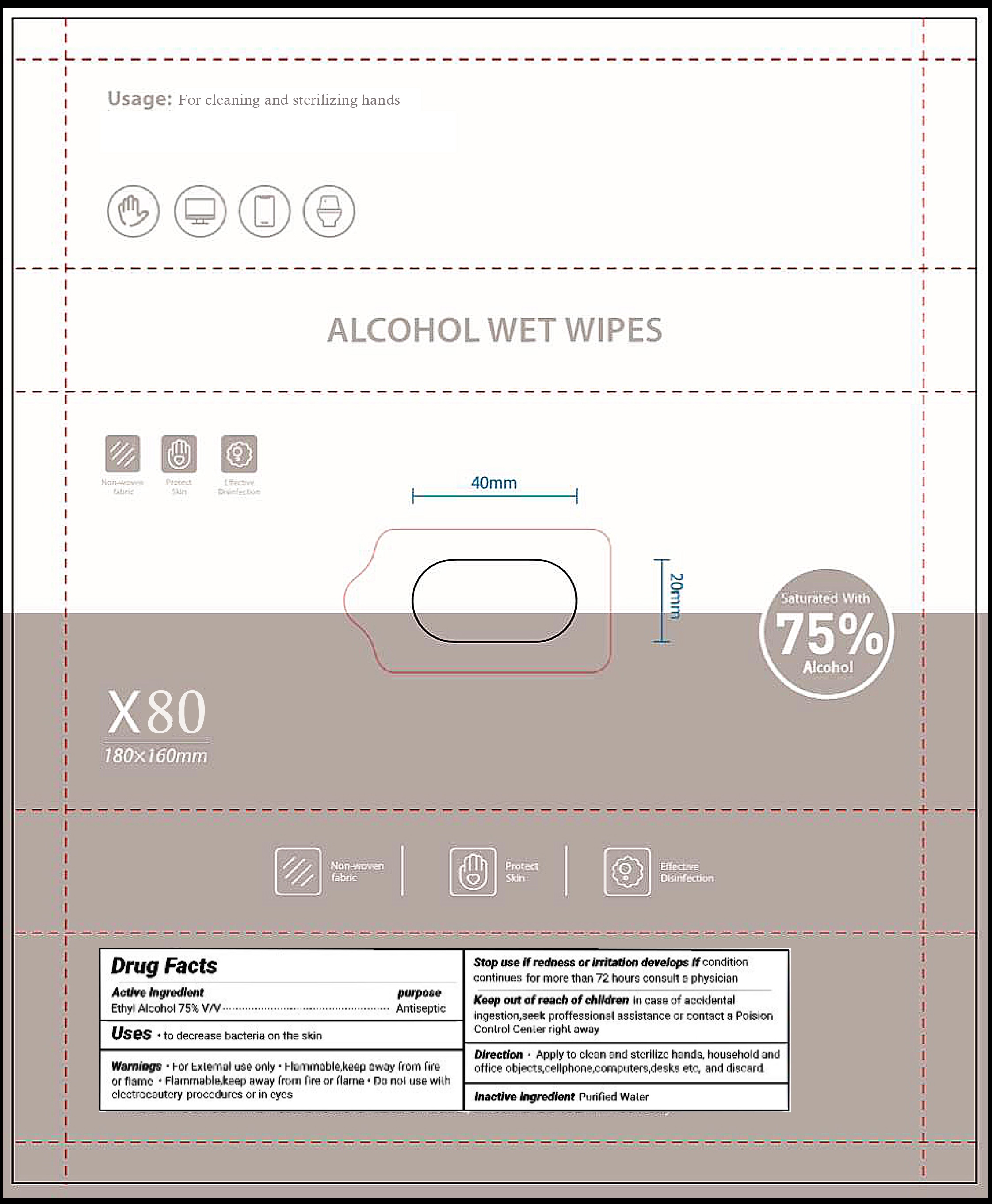 DRUG LABEL: Alcohol Wet Wipes
NDC: 74979-006 | Form: CLOTH
Manufacturer: Robert Gordon Ind. Ltd.
Category: otc | Type: HUMAN OTC DRUG LABEL
Date: 20230327

ACTIVE INGREDIENTS: ALCOHOL 0.75 mL/1 mL
INACTIVE INGREDIENTS: WATER

Alcohol Wet Wipes

Active Ingredient

Ethyl Alcohol 75% (v/v)

purpose

Antiseptic

Uses

- For hand sanitizing to decrease bacteria on the skin

Warnings

- Flammable. Keep away from heat and flame.
- For External use only.

Do not use

- In eyes. In case of contact, rinse thoroughly with water

When Using this product

- avoid contact with eyes and mouth. If in ayes, flush thoroughly with water.
- Discontinue use and contact a doctor if irritation and redness develop and conditions persis for more than 72 hours.

Keep out of reach of children

unless under adult supervision. If swallowed, get medical help or contact a Poison Control Center right away.

Directions

- Tear open packet and remove wipe.
- Wet hands thoroughly with product and let hands air dry.
- Throw used wipe in trash. Do not flush.

Inactive ingredient

Water

Major changes

Uses - to decrease bacteria on the skin

Dosage and administration - Apply to clean and sterilizc hands, household and office objects,cellphone, computers,desks etc, and discard.

Other Information

- Store between 15-30oC (59-86oF)
- Avoid freezing and excessive heat above 40oC (104oF)